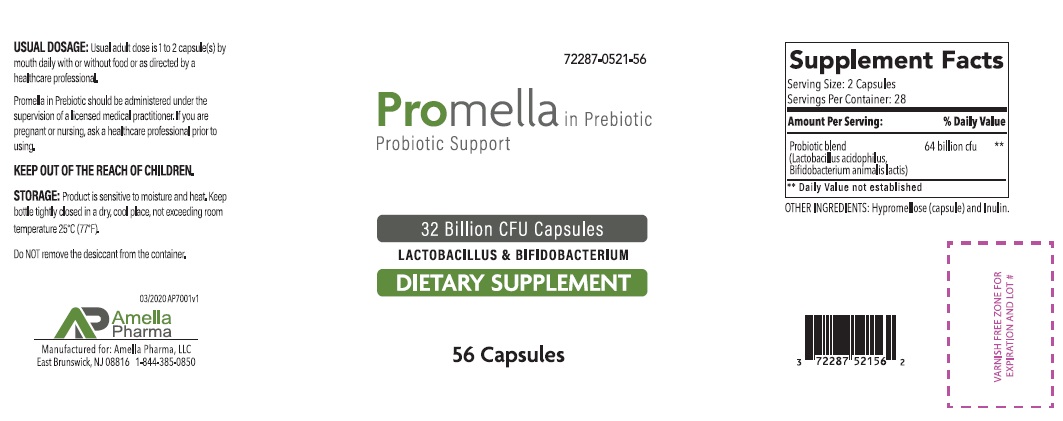 DRUG LABEL: Promella
NDC: 72287-521 | Form: CAPSULE
Manufacturer: Amella Pharma, LLC
Category: other | Type: DIETARY SUPPLEMENT
Date: 20200501

ACTIVE INGREDIENTS: LACTOBACILLUS ACIDOPHILUS 16000000000 [CFU]/1 1; BIFIDOBACTERIUM ANIMALIS LACTIS 16000000000 [CFU]/1 1
INACTIVE INGREDIENTS: HYPROMELLOSE, UNSPECIFIED; INULIN

Promella in Prebiotic Capsules
Dietary Supplement

HEALTH CLAIM:

Promella in Prebiotic Capsules Dietary Supplement
Dispensed by Prescription

Supplement Facts
Serving Size: 2 Capsules
Servings Per Container: 28
Amount Per Serving: | % Daily Value
Probiotic blend; (Lactobacillus acidophilus,; Bifidobacterium animalis lactis) | 64 billion cfu **
** Daily values not established

Other Ingredients: Hypromellose (capsule) and Inulin.

DESCRIPTION

Promella in Prebiotic is an orally administered prescription probiotic formulation for the clinical dietary management of suboptimal nutritional status in patients where advanced supplementation is required and nutritional supplementation in physiologically stressful conditions for maintenance of good health is needed.

Promella in Prebiotic should be administered under the supervision of a licensed medical practitioner.

WARNINGS AND PRECAUTIONS

This product is contraindicated in patients with a known hypersensitivity to any of the ingredients.

Promella in Prebiotic should only be used under the direction and supervision of a licensed medical practitioner. Use with caution in patients that may have a medical condition, are pregnant, lactating, trying to conceive, under the age of 18, or taking medications.

DOSAGE AND ADMINISTRATION

Usual adult dose is 1 to 2 capsule(s) by mouth daily with or without food.

INDICATIONS AND USAGE

Promella in Prebiotic is an orally administered prescription probiotic formulation for the clinical dietary management of suboptimal nutritional status in patients where advanced supplementation is required and nutritional supplementation in physiologically stressful conditions for maintenance of good health is needed.

HOW SUPPLIED:

Promella in Prebiotic is supplied as clear capsules dispensed in HDPE plastic bottles of 56ct.

72287-521-56

Reserved for Professional Recommendation

All prescriptions using this product shall be pursuant to state statutes as applicable. This is not an Orange Book product. This product may be administered only under a physician’s supervision. There are no implied or explicit claims on therapeutic equivalence.

Manufactured for:
Amella Pharma, LLC
East Brunswick, NJ 08816

04/2020 AP7002v1

STORAGE:

Product is sensitive to moisture and heat. Keep bottle tightly closed in a dry, cool place, not exceeding room temperature 25°C (77°F). Call your doctor about side effects. You may report side effects to FDA at 1-800-FDA-1088.

KEEP THIS OUT OF THE REACH OF CHILDREN.

PACKAGE LABEL

Probiotic Support

32 Billion CFU Capsules

Do NOT remove the desiccant from the container.

1-844-385-0850

PACKAGING